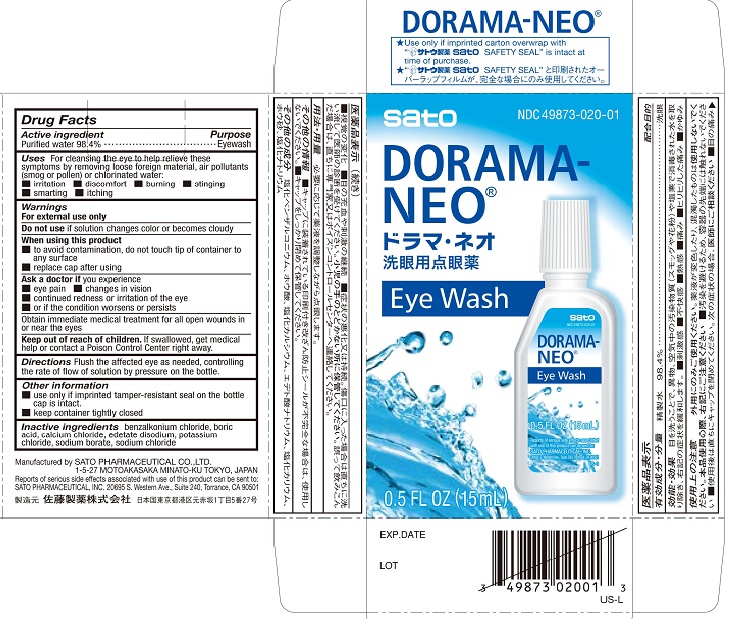 DRUG LABEL: Dorama-Neo
NDC: 49873-020 | Form: LIQUID
Manufacturer: Sato Pharmaceutical Co., Ltd.
Category: otc | Type: HUMAN OTC DRUG LABEL
Date: 20231206

ACTIVE INGREDIENTS: WATER 98.4 mL/100 mL
INACTIVE INGREDIENTS: BENZALKONIUM CHLORIDE; BORIC ACID; CALCIUM CHLORIDE; EDETATE DISODIUM; POTASSIUM CHLORIDE; SODIUM BORATE; SODIUM CHLORIDE

Dorama-Neo

Active ingredient Purified water 98.4%

Purpose Eyewash

INDICATIONS AND USAGE

Uses For cleansing the eye to help relieve these symptoms by removing loose foreign material, air pollutants (smog or pollen) or chlorinated water:
■irritation ■discomfort ■burning ■stinging ■smarting ■itching

Warnings
For external use only

Do not use if solution changes color or becomes cloudy

When using this product
■to avoid contamination, do not touch tip of container to any surface
■replace cap after using

Ask a doctor if you experience
■eye pain ■changes in vision
■continued redness or irritation of the eye
■or if the condition worsens or persists

PRECAUTIONS

Obtain immediate medical treatment for all open wounds in or near the eyes

KEEP OUT OF REACH OF CHILDREN

Keep our of reach of children. If swallowed, get medical help or contact a Poison Control Center right away.

DOSAGE AND ADMINISTRATION

Directions Flush the affected eye as needed, controlling the rate of flow of solution by pressure on the bottle.

INACTIVE INGREDIENT

Inactive ingredients benzalkonium chloride, boric acid, calcium chloride, edetate disodium, potassium chloride, sodium borate, sodium chloride